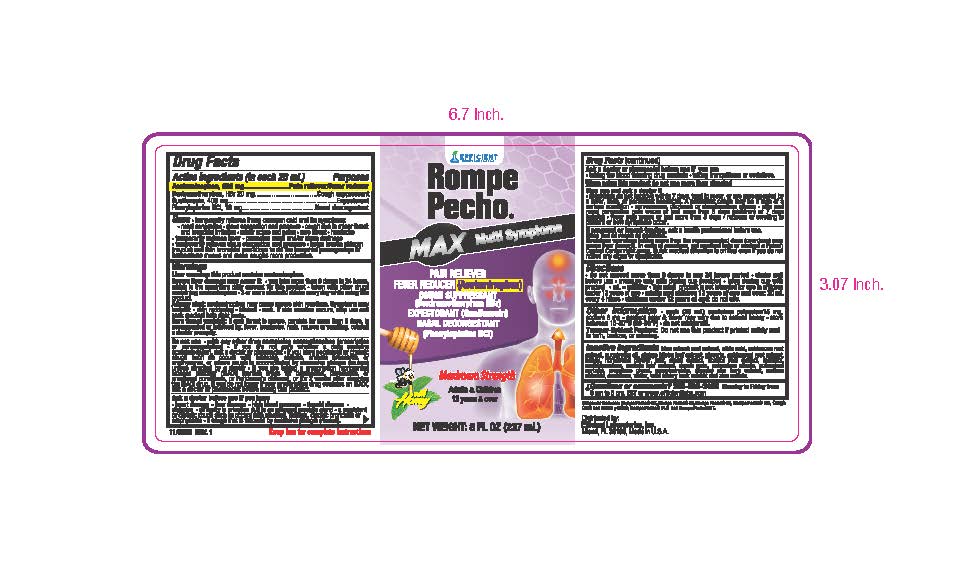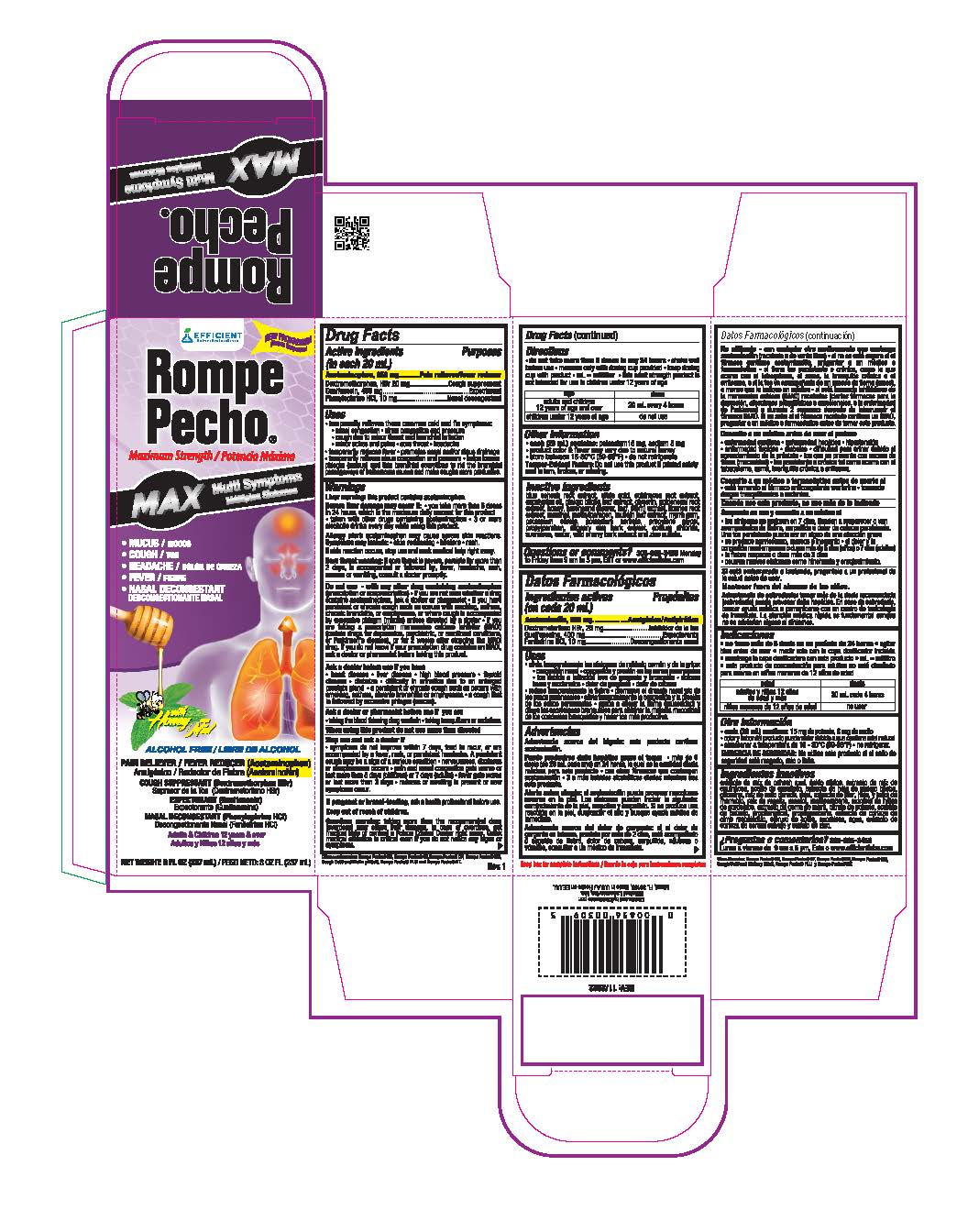 DRUG LABEL: Rompe Pecho Max Multi Symptoms
NDC: 58593-828 | Form: LIQUID
Manufacturer: EFFICIENT LABORATORIES INC
Category: otc | Type: HUMAN OTC DRUG LABEL
Date: 20241107

ACTIVE INGREDIENTS: ACETAMINOPHEN 650 mg/20 mL; DEXTROMETHORPHAN HYDROBROMIDE 20 mg/20 mL; GUAIFENESIN 400 mg/20 mL; PHENYLEPHRINE HYDROCHLORIDE 10 mg/20 mL
INACTIVE INGREDIENTS: WATER; PRUNUS SEROTINA BARK; ZINC SULFATE; CAULOPHYLLUM THALICTROIDES ROOT; CITRIC ACID MONOHYDRATE; ECHINACEA, UNSPECIFIED; EUCALYPTUS OIL; GINKGO; GLYCERIN; GOLDENSEAL; HONEY; HOREHOUND; LICORICE; MENTHOL; METHYLPARABEN; MULLEIN LEAF; MYRRH; POTASSIUM CITRATE; POTASSIUM SORBATE; PROPYLENE GLYCOL; PROPYLPARABEN; ULMUS RUBRA BARK; SODIUM CHLORIDE; SUCRALOSE

Active ingredients Purposes

(in each 20mL)

Acetaminophen 650 mg..................................Pain reliever/feverreducer

Dextromethorphan Hbr 20 mg............................Cough suppressant

Guaifenesin 400 mg...........................................Expectorant

Phenylephtine HCl 10 mg...................................Nasal decongestant

PURPOSE

- Pain reliever/fever reducer
- Cough suppressant
- Expectorant
- Nasal decongestant

Uses

- temprarily relieves these common cold and flu symptoms:
- nasal congestion
- sinus congestion and pressure
- cough due to minor throat and bronchial irritation
- minor aches and pains
- sore throat
- headache
- temporarily reduces fever
- promotes nasal and/or sinus drainage; temporarily relieves sinus congestion and pressure
- helps loosen phlegm (mucus) and thin bronchial secretions to rid the bronchial passageways of bothersome mucus and make coughs more productive

Warning

Liver warning: this product contains acetaminophen.

Severe liver damage may occur if:

- you take more than 6 doses in 24 hours, which is the maximum daily amount for this product
- taken with other drugs containing acetaminophen
- 3 or more alcoholic drinkss every day while using this product.

Allergy alert: acetaminophen may cause severe skin reactions. Symptoms may include: • skin reddening • blisters • rash.

If skin reaction occurs, stop use and seek medical help right away.

Sore throat warning: if sore throat is severe, persists for more than 2 days, is accompanied or followed by, fever, headahce, rash, nausea or vomiting, consult a doctor promtly.

Do not use

- with any other drug containing acetaminophen (prescription or nonprescription).
- if you are not sure whether a drug contains acetaminophen, ask a doctor or a pharmacist.
- if you have persistent or chronic cough such as occurs with smoking, asthma, chronic bronchitis, or emphysema, or where cough is accompanied by excessive phlegm (mucus) unless directed by a doctor.
- If you are taking a prescription monoamine oxidase inhibitor (MAOI) (certain drugs for depression, psychiatric, or emotional conditions, or Parkinson's disease), or for 2 weeks after stopping the MAOI drug. If you do not know if your prescription drug contains an MAOI, ask a doctor or pharmamcist before taking this product.

Ask a doctor before use if you have

- heart disease
- liver disease
- high blood pressure
- thyroid disease
- diabetes
- difficulty in urination due to an enlarged prostate gland
- a persistent or chronic cough such as occurs with smoking, asthma, chronic bronchitis or emphysema.
- a cough that is followed by excessive phlegm (mucus)

Ask a docotor or pharmacist before use if you are

- taking the blood thinning drug warfarin
- taking tranquilizers or sedatives

When using this product do not use more than directed

Stop use and ask a doctor if

- symptoms do not improve within 7 days, tend to recur, or are accompanied by a fever, rash or persistent headache. A persistent cough may be a sign of a serious condition
- nervousness, dizziness or sleeplessness occurs
- pain and nasal congestion gets worse or last more than 5 days (children) or 7 days (adults)
- fever gets worse or last more than 3 days
- redness or swelling is present or new symptoms occur.

PREGNANCY OR BREAST FEEDING

If pregnant or breast-feeding, ask a health professional before use.

Keep out of reach of children.

OVERDOSAGE

Overdose warning: taking more than the recommended dose (overdose) may cause liver damage. In case of overdose, get medical help or contact a Poison Control Center right away. Quick medical attention is critical even if you do not notice any signs or symptoms.

Directions

- do not take more than 6 doses in any 24 hours
- shake well before use
- measure only with dosing cup provided
- keep dosing cup with product
- mL = milliliter
- this adult strength product is not intended for use in children under 12 years of age

age | dose
adults and children 12 years of age and over | 20 mL every 4 hours
children under 12 years of age | do not use

Inactive ingreadients:

Blue cohosh root extract, citirc acid, echinacea root extract, eucalptus oil, ginko biloba leaf extract, glycerin, goldenseal root extract, honey, horehound (flower, leaf, stem) extract, licorice root extract, menthol, methylparaben, mullein leaf extract, myrrh gum, potassium citrate, potassium sorbate, propylene glycol, propylparaben, slippery elm bark extract, sodium chloride, suralose, water, wild cherry bark extract and zinc sulfate.

Questions or comments?

(305) 805-3456 Monday to Friday from 9 am to 5 pm EST or www.efficientlabs.com

RECENT MAJOR CHANGES

Recommendations should be added in the Directions section, such as:

• do not take more 6 doses in any 24 hours

• measure only with dosing cup provided

• keep dosing cup with product

• mL= milliliter

• this strength product is not intended for use in children under 12 years of age

Typographical adjustments were made, and clarity was provided on the dosage by age through a table:

age | dose
adults and children 12 years of age and over | 20 mL every 4 hours
children under 12 years of age | do not use